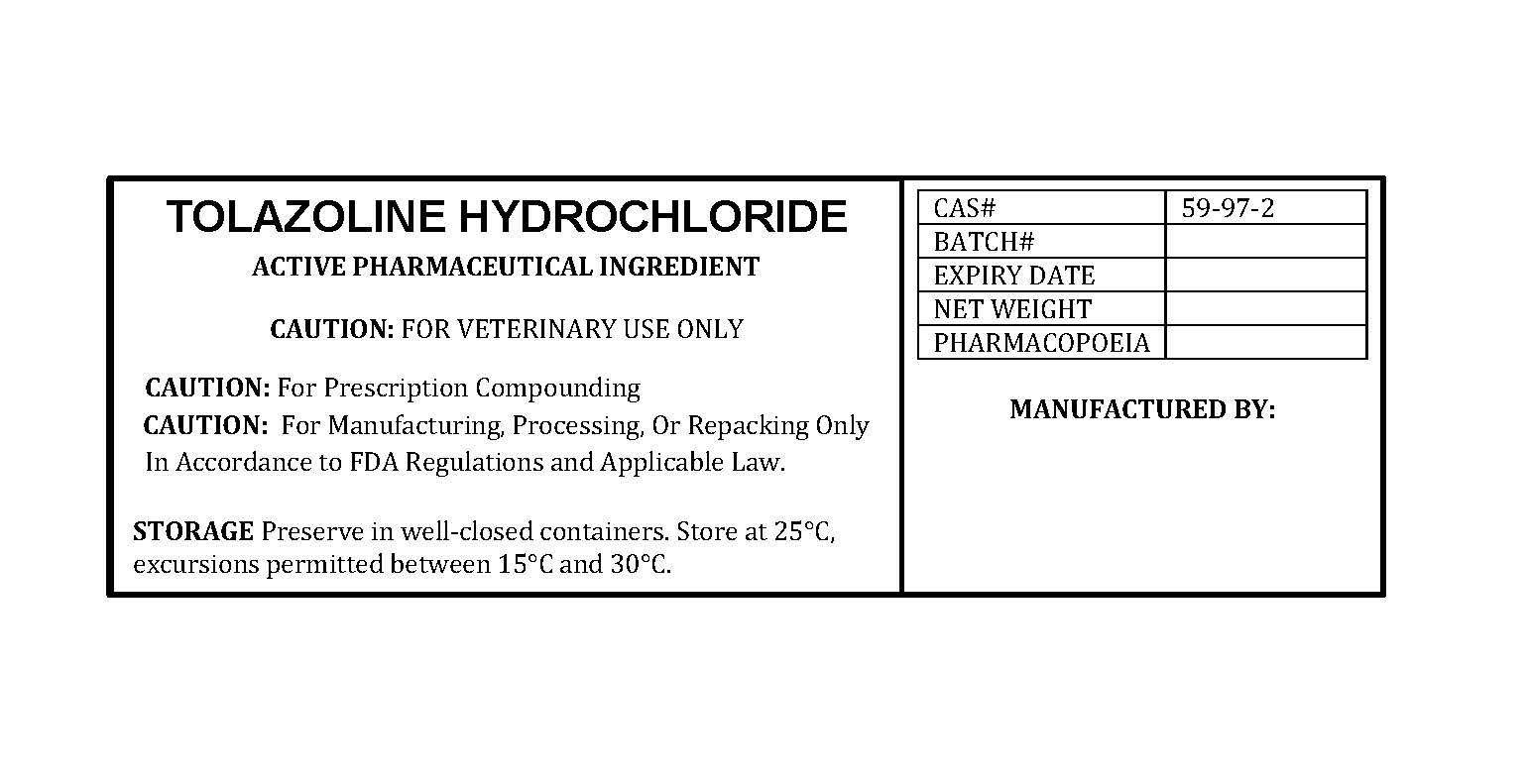 DRUG LABEL: TOLAZOLINE HYDROCHLORIDE
NDC: 86184-390 | Form: POWDER
Manufacturer: MAEDA INC
Category: other | Type: BULK INGREDIENT - ANIMAL DRUG
Date: 20250820

ACTIVE INGREDIENTS: TOLAZOLINE HYDROCHLORIDE 1 g/1 g

TOLAZOLINE HYDROCHLORIDE

PACKAGE LABEL

tolazolinehydrochloridelabelfile.jpg